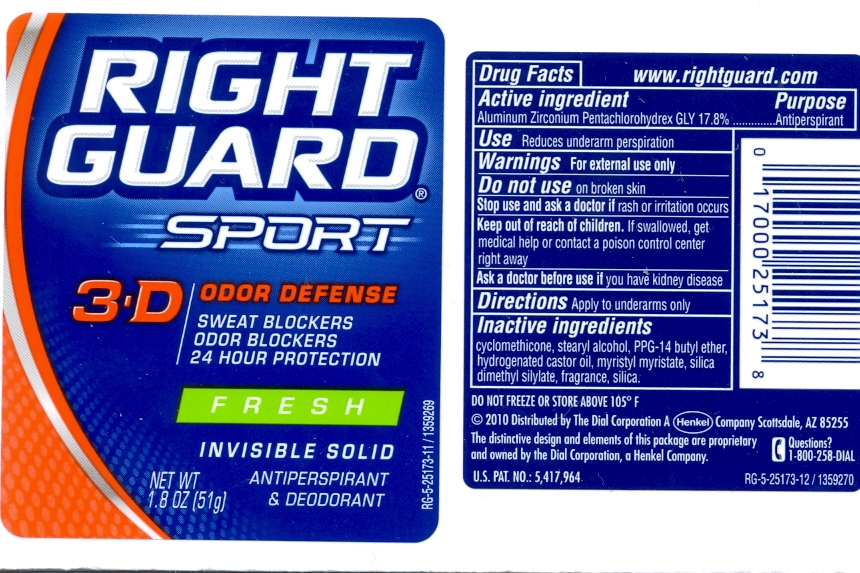 DRUG LABEL: RG Sport Inv.Solid Antiperspirant Deodorant Fresh
NDC: 54340-068 | Form: STICK
Manufacturer: The Dial Corporation
Category: otc | Type: HUMAN OTC DRUG LABEL
Date: 20110414

ACTIVE INGREDIENTS: Aluminum Zirconium Pentachlorohydrex Gly 14.062 g/79 g
INACTIVE INGREDIENTS: CYCLOMETHICONE 5 33.25608 g/51 g; STEARYL ALCOHOL 10.2 g/51 g; PPG-14 BUTYL ETHER 4.998 g/51 g; HYDROGENATED CASTOR OIL 1.4484 g/51 g; MYRISTYL MYRISTATE 0.9792 g/51 g

Right Guard Sport Invisible Solid Antiperspirant Deodorant Fresh, 3-D Odor Defense

ACTIVE INGREDIENT

Aluminum Zirconium Pentachlorohydrex Gly 17.8%

PURPOSE

Antiperspirant

INDICATIONS AND USAGE

Use: Reduces underarm perspiration

Warnings: For external use only.

Do not use on broken skin.

Stop use and ask a doctor if rash or irritation occurs.

Keep out of reach of children. If swallowed, get medical help or contact a poison control center right away.

Ask a doctor before use if you have kidney disease.

DOSAGE AND ADMINISTRATION

Directions: Apply to underarms only.

INACTIVE INGREDIENT

Cyclomethicone, stearyl alcohol, PPG-14 butyl ether, hydrogenated castor oil, myristyl myristate, silica, dimethyl silylate, fragrance, silica.

STORAGE AND HANDLING

DO NOT FREEZE OR STORE ABOVE 105°F

HOW SUPPLIED

2010 Distributed by The Dial Corporation A Henkel Company Scottsdale, AZ, 85255. The distinctive design and elements of this package are proprietary and owned by the Dial Corporation, a Henkel Company. U.S.PAT.NO.:5,417,964

Questions? 1-800-258-DIAL